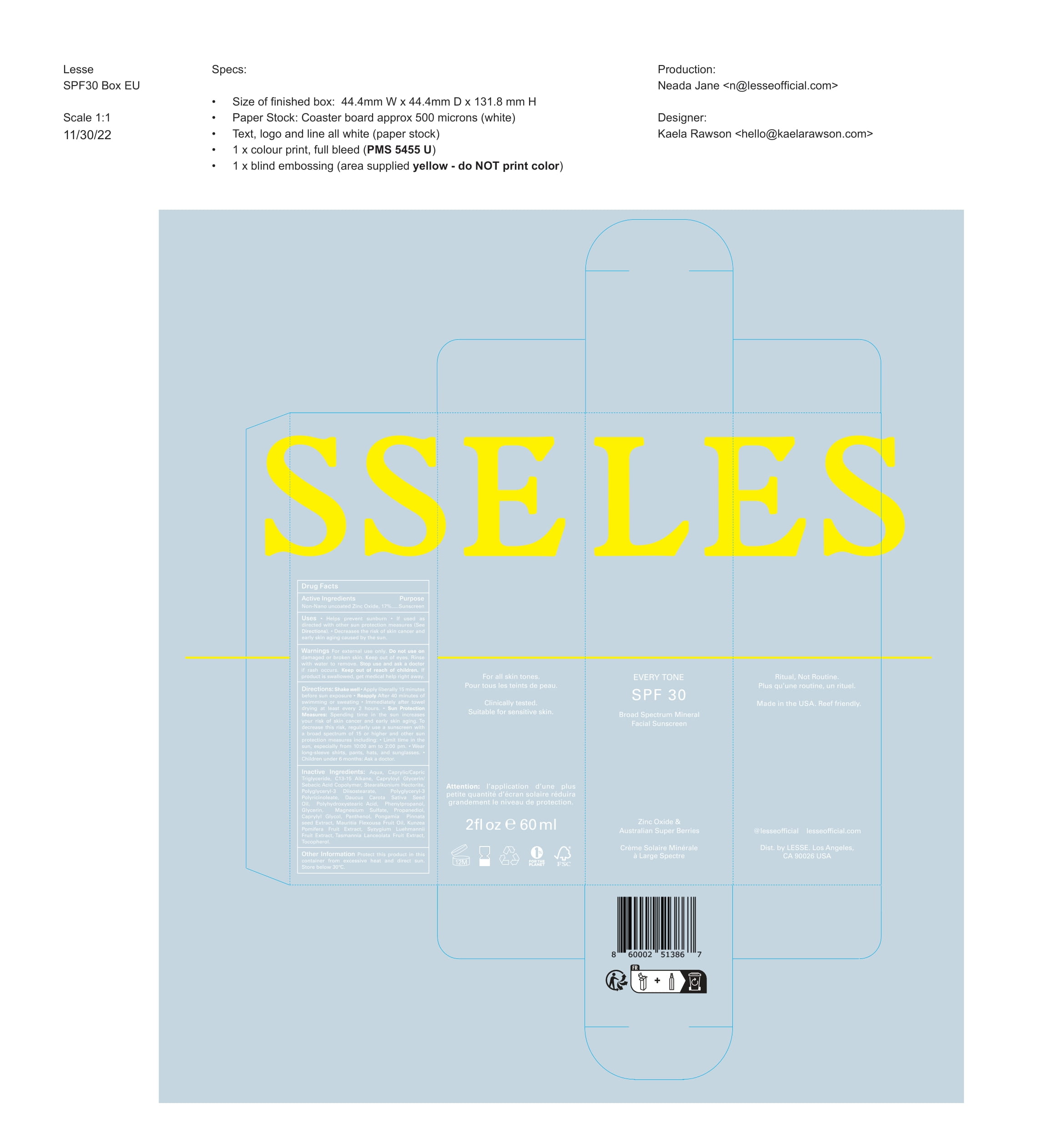 DRUG LABEL: LESS EVERY TONE SPF 30
NDC: 73964-032 | Form: LOTION
Manufacturer: Happy Farm Botanicals
Category: otc | Type: HUMAN OTC DRUG LABEL
Date: 20251006

ACTIVE INGREDIENTS: ZINC OXIDE 17 g/100 g
INACTIVE INGREDIENTS: C13-15 ALKANE 17 g/100 g; POLYGLYCERYL-3 DIISOSTEARATE 1.5 g/100 g; POLYGLYCERYL-3 RICINOLEATE 1.5 g/100 g; CAPRYLYL GLYCOL 0.375 g/100 g; PONGAMIA PINNATA SEED 0.25 g/100 g; GLYCERIN 0.6 g/100 g; TASMANNIA LANCEOLATA FRUIT 0.05 g/100 g; MAURITIA FLEXUOSA FRUIT OIL 0.2 g/100 g; POLYHYDROXYSTEARIC ACID (2300 MW) 0.75 g/100 g; WATER 40.25 g/100 g; KUNZEA POMIFERA FRUIT 0.05 g/100 g; SYZYGIUM LUEHMANNII FRUIT 0.05 g/100 g; CAPRYLIC/CAPRIC/LINOLEIC TRIGLYCERIDE 13.75 g/100 g; STEARALKONIUM HECTORITE 2 g/100 g; MAGNESIUM SULFATE ANHYDROUS 0.5 g/100 g; PHENYLPROPANOL 0.72 g/100 g; PROPANEDIOL 0.405 g/100 g; DAUCUS CAROTA SUBSP. SATIVUS SEED 0.8 g/100 g; CAPRYLOYL GLYCERIN/SEBACIC ACID COPOLYMER (2000 MPA.S) 2 g/100 g; PANTHENOL 0.25 g/100 g

Sunscreen Product Listing

Active Ingredients Section

Active Ingredients Purpose

Non-Nano uncoated Zinc Oxide, 17% Sunscreen

Purpose

Sunscreen

Uses

- Helps prevent sunburn
- If used as directred with other sunprotection measures (See Directions).

Decrease the risk of skin cancer and early skin aging caused by the sun.

Warnings

- For external use only
- Do not use on damage or broken skin
- When using the product keep out of eyes. Rinse with water to remove.
- Stop use and ask a doctor if rash occurs
- Keep out of reach of children, If product is swallowed, get medical help or contact a Poison Control Center right away.

Do not use on damage or broken skin

When using this product keep out of eyes. Rinse with water to remove.

Stop use and ask a doctor if rash occurs

Keep out of reach of children. If product is swallowed, get medical help or contact

Directions

- Shake well
- Apply Liberally 15 minutes before sun exposure
- Reapply:
- After 40 minutes of swimming or sweating
- Immediately after towel drying
- at least every 2 hours
- Sun Protection Measures. Spending time in the sun increases your risk of skin cancer and early skin aging. To decrease this risk, regularly use a sunscreen with a broad specfgtrum of 15 or higher and other sun protection measures including:
- Limit time in the sun, espcially from 10:00 am - 2:00 pm.
- Wear long-sleeve shirts, pants, hats, and sunglasses.
- Children under 6 months: Ask a doctor

Inactive Ingredients

Water, Caprylic/Capric Triglycerides, C13-15 Alkane, Caproyl Glycerin/Sebacic Acid Copolymer, Stearalkonium Hectorite, Polyglyceryl-3 Diisostearate, Polyglyceryl-3 Polyricinoleate, Daucus Carota Sativa Seed Oil, Polyhydroxystearic Acid, Phenylpropanol, Glycerin, Magnesium Sulfate, Propanediol, Caprylyl Glycol, Panthenol, Pongamia Pinnata seed Extract, Mauritia Flexousa Fruit Oil, Kunzea Pomifera Fruit Extract, Syzygium Luehmannii Fruit Extract, Tasmannia Lanceolata Fruit Extract, Tocophderol.

Other Information

- Protecrt this product in this container from excessive heat and direct sun

PACKAGE LABEL

LESSE

EVERY TONE SPF 30

Broad Spectrum Mineral Facial Sunscreen

Zinc Oxide & Australian Super Berries

Creme Solaire Minerale a Large Spectre

SPF 30 Contro Elementi Quotidiani

Mineralischer Breitband-Sonnenschutz

Solcreme| Minerale Zonnebrandcreme

Oxyde de zinc et plantes reparatrices